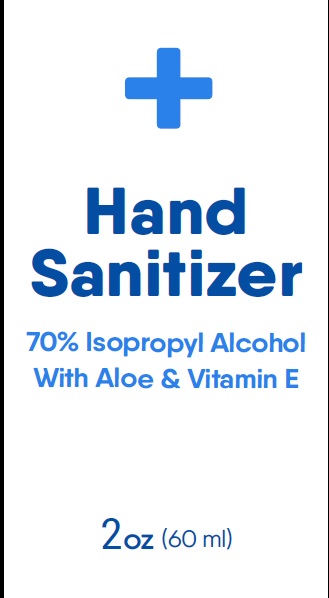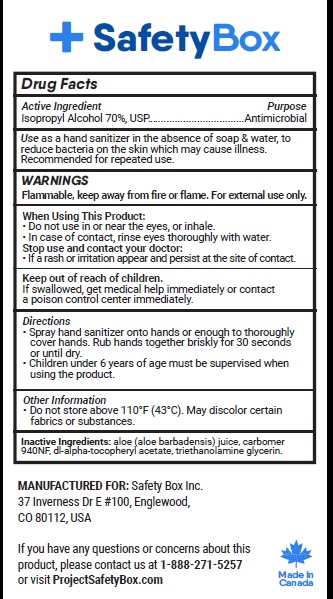 DRUG LABEL: Hand Sanitizer
NDC: 79670-001 | Form: LIQUID
Manufacturer: 12016133 Canada Inc
Category: otc | Type: HUMAN OTC DRUG LABEL
Date: 20200713

ACTIVE INGREDIENTS: ISOPROPYL ALCOHOL 70 mL/100 mL
INACTIVE INGREDIENTS: ALOE VERA LEAF; CARBOMER 940; .ALPHA.-TOCOPHEROL ACETATE; TROLAMINE; GLYCERIN

Active Ingredient

Isopropyl Alcohol 70%, USP

Purpose

Antimicrobial

Uses

Use as a hand sanitizer in the absence of soap and water, to reduce bacteria on the skin which may cause illness.

Recommended for repeated use.

Warnings

For external use only. Flammable. Keep away from heat or flame.

When Using This Product:

- Do not use in or near the eyes, or inhale.
- In case of contact, rinse eyes thoroughly with water.

Stop use and contact your doctor if a rash or irritation appear and persist at the site of contact.

Keep out of reach of children. If swallowed, get medical help immediately or contact a poison control center immediately.

Directions

- Spray hand sanitizer onto hands or enough to thoroughly cover hands. Rub hands together briskly for 30 seconds or until dry.
- Children under 6 years of age must be supervised when using the product

Other information

- Do not store above 110°F (43°C). May discolor certain fabrics or substances.

Inactive ingredients

aloe (aloe barbadensis) juice, carbomer 940NF, dl-alpha-tocopheryl acetate, triethanolamine glycerin.